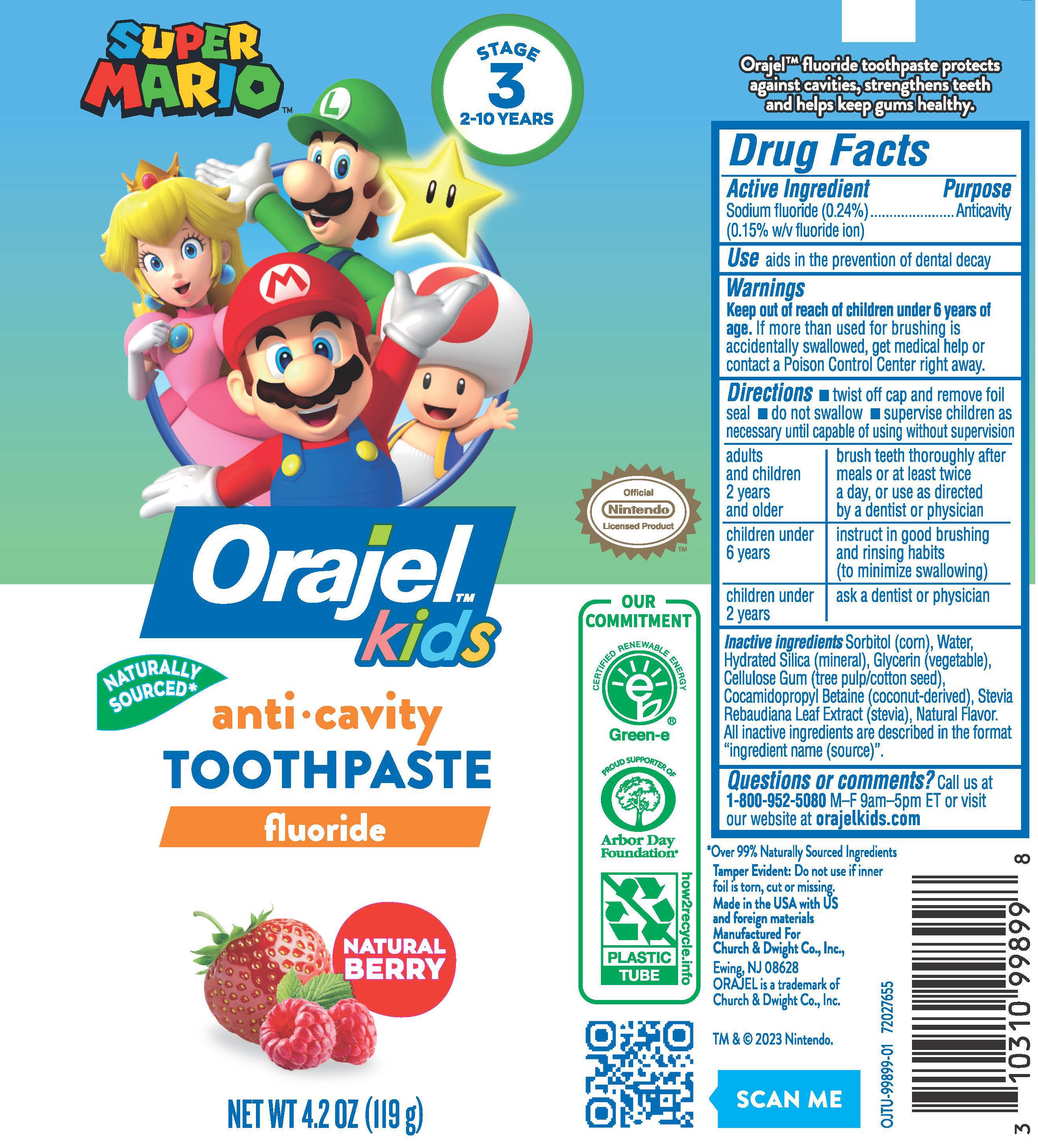 DRUG LABEL: Orajel SuperMario
NDC: 10237-733 | Form: PASTE, DENTIFRICE
Manufacturer: Church & Dwight Co., Inc.
Category: otc | Type: HUMAN OTC DRUG LABEL
Date: 20241126

ACTIVE INGREDIENTS: SODIUM FLUORIDE 2.4 mg/1 g
INACTIVE INGREDIENTS: GLYCERIN; STEVIA REBAUDIANA LEAF/STEM EXTRACT; CELLULOSE GUM; WATER; SORBITOL; COCAMIDOPROPYL BETAINE; HYDRATED SILICA

Orajel Kids Super Mario Anticavity Toothpaste

ACTIVE INGREDIENT

Sodium fluoride (0.24%) (0.15% w/v fluoride ion)

PURPOSE

Anticavity

USE

aids in the prevention of dental decay

WARNING

Keep out of reach of children under 6 years of age. If more than used for brushing is accidentally swallowed, get medical help or contact a Poison Control Center right away.

DIRECTIONS

■ twist off cap and remove foil seal ■ do not swallow ■ supervise children as necessary until capable of using wilhout supervision

adults and children 2 years and older: brush teeth thoroughly after meals or at least twice a day, or use as directed by a dentist or physician

children under 6 years: instruct in good brushing and rinsing habits (to minimize swallowing)
children under 2 years: ask a dentist or physician

INACTIVE INGREDIENTS

Sorbitol (corn), Water, Hydrated Silica (mineral), Glycerin (vegetable), Cellulose Gum (tree pulp/cotton seed), Cocamidopropyl Betaine (coconut-derived), Stevia Rebaudiana Leaf Extract (stevia), Natural flavor.
All inactive ingredients are described in the format "ingredient name (source)".

PACKAGE LABEL

SUPER MARIO

STAGE 3

2-10 YEARS

ORAJELTM KIDS

anti-cavity

TOOTHPASTE

fluoride

NATURALLY SOURCED*

NATURAL BERRY

NET WT 4.2 OZ (119 g)